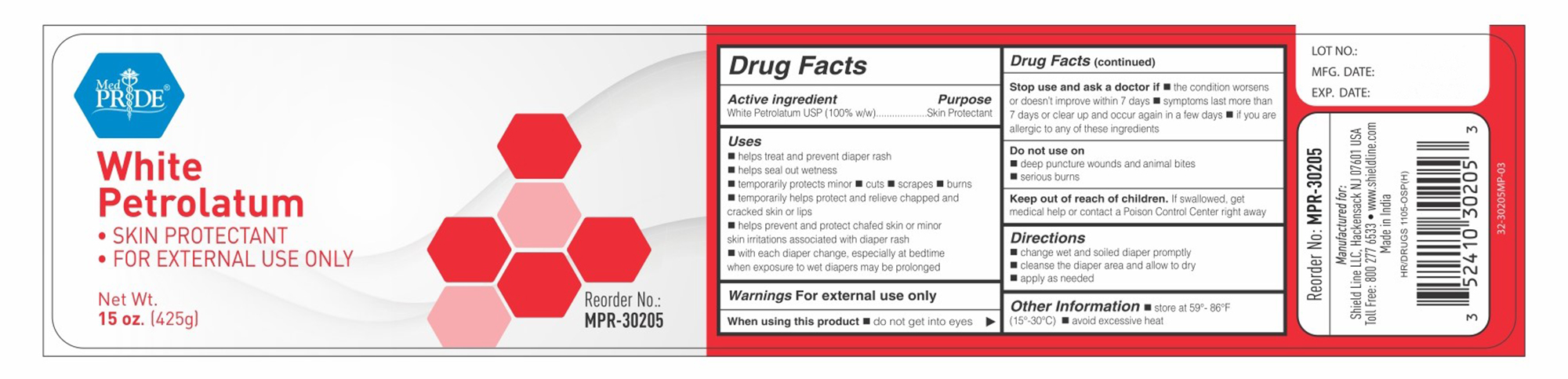 DRUG LABEL: Medpride
NDC: 52410-3020 | Form: OINTMENT
Manufacturer: Shield Line LLC
Category: otc | Type: HUMAN OTC DRUG LABEL
Date: 20250818

ACTIVE INGREDIENTS: PETROLATUM 100 g/100 g
INACTIVE INGREDIENTS: WATER

MedPride White Petrolatum

Active Ingredient

White Petroleum Jelly USP [100% w/w]

Purpose

Skin Protectant

Uses

■ helps treat and prevent diaper rash ■ helps seal out wetness ■ temporarily protects minor ■ cuts ■ scrapes ■ burns ■ temporarily helps protect and relieve chapped and cracked skin or lips ■ helps prevent and protect chafed skin or minor skin irritations associated with diaper rash ■ with each diaper change, espicially at bedtime when exposure to wet diapers may be prolonged

Warnings

For external use only

When using this product

■ do not get into eyes

Stop use and ask a doctor if

■ condition worsens ■ symptoms last more than 7 days or clear up and occur again in a few days

Do not use on

■ deep puncture woulnd ■ animal bites ■ serious burns

Keep out of reach of children. If swallowed, get medical help or contact a Poison Control Center right away

Directions

■ change wet and soiled diapers promptly ■ cleanse the diaper area and allow to dry ■ apply as needed

Other Information

■ store at 59-86F (15-30C) ■ avoid excessive heat

Inactive Ingredient

None